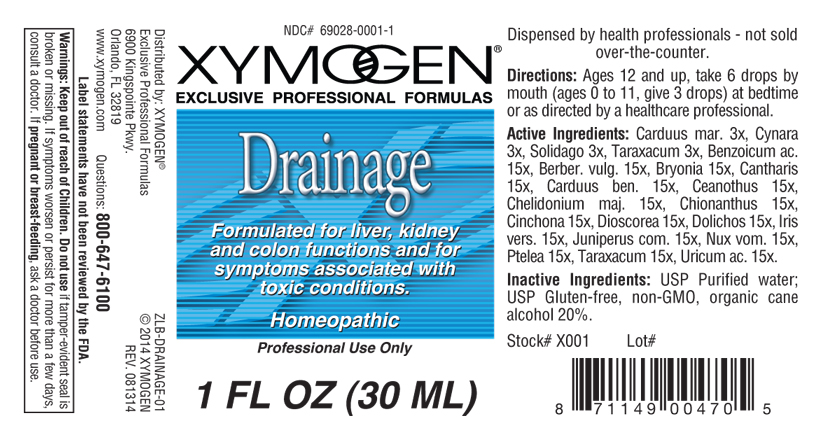 DRUG LABEL: Drainage 
NDC: 69028-0001 | Form: LIQUID
Manufacturer: Xymogen
Category: homeopathic | Type: HUMAN PRESCRIPTION DRUG LABEL
Date: 20140929

ACTIVE INGREDIENTS: Benzoic Acid 15 [hp_X]/1 mL; Berberis Vulgaris Root Bark 15 [hp_X]/1 mL; Bryonia Alba Root 15 [hp_X]/1 mL; Lytta Vesicatoria 15 [hp_X]/1 mL; Centaurea Benedicta 15 [hp_X]/1 mL; Ceanothus Americanus Leaf 15 [hp_X]/1 mL; Chelidonium Majus 15 [hp_X]/1 mL; Chionanthus Virginicus Bark 15 [hp_X]/1 mL; Cinchona Officinalis Bark 15 [hp_X]/1 mL; Dioscorea Villosa Tuber 15 [hp_X]/1 mL; Mucuna Pruriens Fruit Trichome 15 [hp_X]/1 mL; Iris Versicolor Root 15 [hp_X]/1 mL; Juniper Berry 15 [hp_X]/1 mL; Strychnos Nux-vomica Seed 15 [hp_X]/1 mL; Ptelea Trifoliata Bark 15 [hp_X]/1 mL; Taraxacum Officinale 15 [hp_X]/1 mL; Uric Acid 15 [hp_X]/1 mL; Silybum Marianum Seed 3 [hp_X]/1 mL; Cynara Scolymus Leaf 3 [hp_X]/1 mL; Solidago Virgaurea Flowering Top 3 [hp_X]/1 mL
INACTIVE INGREDIENTS: Alcohol

Drainage

INDICATIONS & USAGE SECTION

Drainer: Formulated for liver, kidney and colon functions and for symptoms associated with toxic conditions.

DOSAGE & ADMINISTRATION SECTION

Directions: Ages 12 and up, take 6 drops by mouth (ages 0 to 11, give 3 drops) at bedtime or as directed by a healthcare professional.

ACTIVE INGREDIENT SECTION

Carduus mar. 3x, Cynara 3x, Solidago 3x, Taraxacum 3x. Benzoicum ac.,15x, Berber. vulg. 15x, Bryonia 15x, Cantharis 15x, Carduus ben.,15x, Ceanothus 15x, Chelidonium maj., 15x, Chionanthus 15x, Cinchona 15x, Dioscorea 15x, Dolichos 15x, Iris vers., 15x, Juniperus com.15x, Nux vom. 15x, Ptelea 15x, Taraxacum 15x, Uricum ac., 15x.

INACTIVE INGREDIENT SECTION

Inactive Ingredients: USP Purified water; USP Gluten-free, non-GMO, organic cane alcohol 20%.

QUESTIONS? SECTION

www.xymogen.com; 6900 Kingspointe Pkwy, Orlando FL 32819 Questions: 800 647- 6100

WARNINGS SECTION

Warning: Keep our of reach of children. Do not use if tamper - evident seal is broken or missing. If symptoms worsen or persist for more than a few days consult a doctor. If pregnant or breast-feeding, ask a doctor before use.

PREGNANCY OR BREAST FEEDING SECTION

If pregnant or breast-feeding, ask a doctor before use.

KEEP OUT OF REACH OF CHILDREN SECTION

Keep out of reach of children.